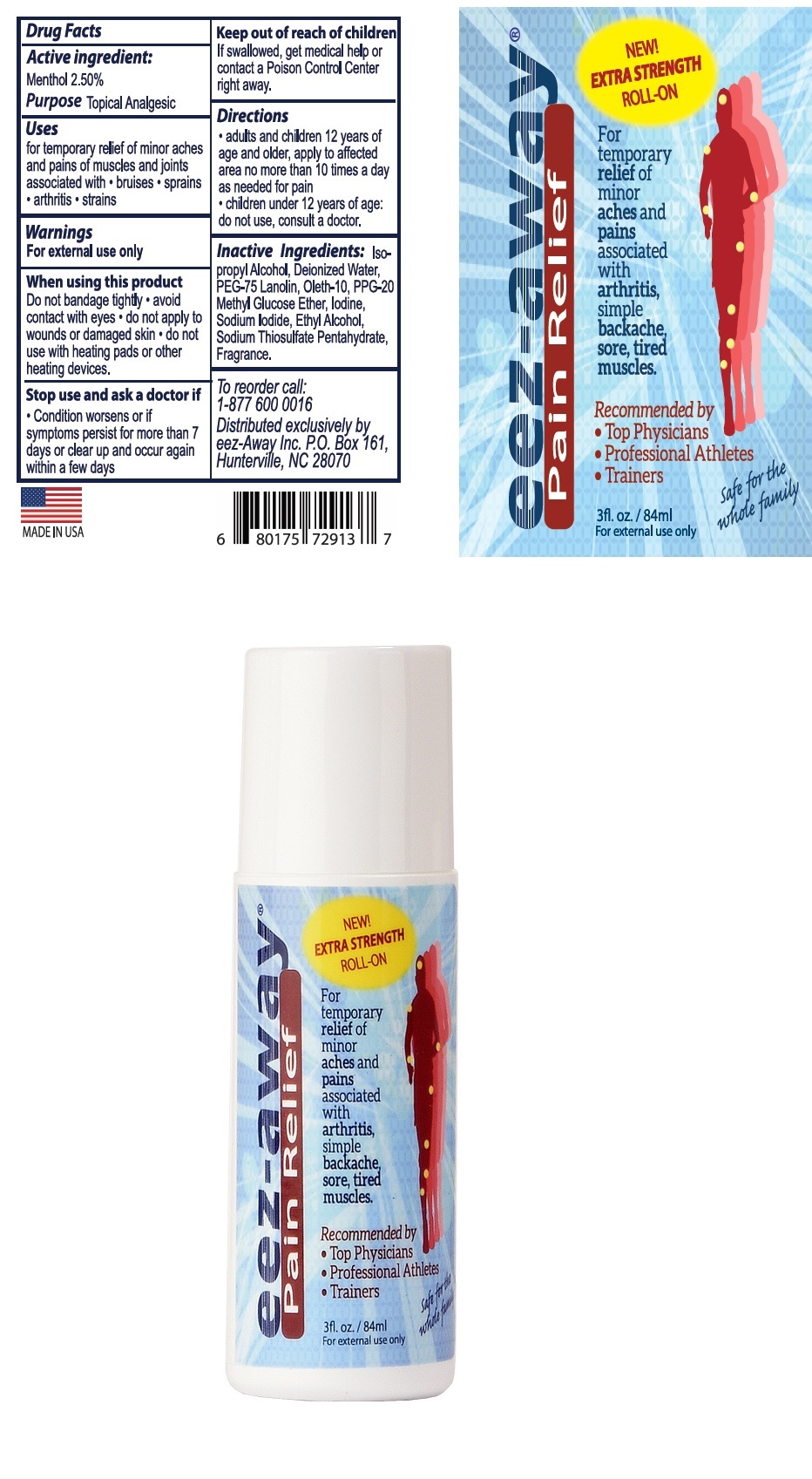 DRUG LABEL: eez-away Pain Relief
NDC: 69678-111 | Form: LIQUID
Manufacturer: EEZAWAY RELIEF INC
Category: otc | Type: HUMAN OTC DRUG LABEL
Date: 20181109

ACTIVE INGREDIENTS: MENTHOL, UNSPECIFIED FORM 2.5 g/100 mL
INACTIVE INGREDIENTS: ISOPROPYL ALCOHOL; WATER; PEG-75 LANOLIN; POLYOXYL-10 OLEYL ETHER; PPG-20 METHYL GLUCOSE ETHER; IODINE; SODIUM IODIDE; ALCOHOL; SODIUM THIOSULFATE

eez-away Pain Relief

Active ingredient:

Menthol 2.50%

Purpose

Topical Analgesic

Uses

for temporary relief of minor aches and pains of muscles and joints associated with • bruises • sprains • arthritis • strains

Warnings:

For external use only

When using this product

Do not bandage tightly • avoid contact with eyes • do not apply to wounds or damaged skin • do not use with heating pads or other heating devices.

Stop use and ask a doctor if

• Condition worsens or if symptoms persist for more than 7 days or clear up and occur again within a few days

Keep out of reach of children.

If swallowed, get medical help or contact a Poison Control Center right away.

Directions

• adults and children 12 years of age and older: apply to affected area no more than 10 times a day as needed for pain.

• children under 12 years of age: do not use, consult a doctor.

Inactive ingredients:

Isopropyl Alcohol, Deionized Water, PEG-75 Lanolin, Oleth-10, PPG-20 Methyl Glucose Ether, Iodine, Sodium Iodide, Ethyl Alcohol, Sodium Thiosulfate Pentahydrate, Fragrance.

QUESTIONS

To reorder call:

1-877 600 0016

NEW! EXTRA STRENGTH ROLL-ON

Recommended by

- Top Physicians
- Professional Athletes
- Trainers

Distributed exclusively by

eez-Away Inc. P.O. Box 161, Hunterville, NC 28070